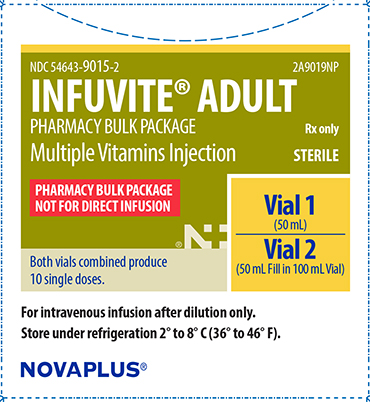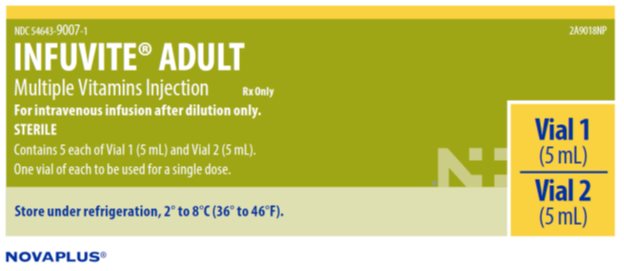 DRUG LABEL: Adult Infuvite Multiple Vitamins
NDC: 54643-9015 | Form: INJECTION, SOLUTION
Manufacturer: Sandoz Inc
Category: prescription | Type: HUMAN PRESCRIPTION DRUG LABEL
Date: 20161028

ACTIVE INGREDIENTS: ASCORBIC ACID 200 mg/10 mL; VITAMIN A PALMITATE 3300 [iU]/10 mL; CHOLECALCIFEROL 200 [iU]/10 mL; THIAMINE HYDROCHLORIDE 6 mg/10 mL; RIBOFLAVIN 5'-PHOSPHATE SODIUM 3.6 mg/10 mL; PYRIDOXINE HYDROCHLORIDE 6 mg/10 mL; NIACINAMIDE 40 mg/10 mL; DEXPANTHENOL 15 mg/10 mL; .ALPHA.-TOCOPHEROL ACETATE 10 [iU]/10 mL; PHYTONADIONE 150 ug/10 mL; FOLIC ACID 600 ug/10 mL; BIOTIN 60 ug/10 mL; CYANOCOBALAMIN 5 ug/10 mL
INACTIVE INGREDIENTS: POLYSORBATE 80; PROPYLENE GLYCOL; ANHYDROUS CITRIC ACID; SODIUM CITRATE, UNSPECIFIED FORM; SODIUM HYDROXIDE; HYDROCHLORIC ACID; WATER

HIGHLIGHTS OF PRESCRIBING INFORMATION

These highlights do not include all the information needed to use INFUVITE ADULT safely and effectively. See full prescribing information for INFUVITE ADULT
INFUVITE ADULT (multiple vitamins injection), for intravenous use
Initial U.S. Approval: 2003

1 INDICATIONS AND USAGE

INFUVITE ADULT is a combination of vitamins indicated for prevention of vitamin deficiency in adults and children aged 11 and older receiving parenteral nutrition (1)

2 DOSAGE AND ADMINISTRATION

- INFUVITE ADULT is a combination product that contains the following vitamins: ascorbic acid, vitamin A, vitamin D, thiamine, riboflavin, pyridoxine, niacinamide, dexpanthenol, vitamin E, vitamin K1, folic acid, biotin, and vitamin B12 (2.1)
- INFUVITE ADULT is for administration by intravenous infusion after dilution (2.1)
- Recommended daily dosage is 10 mL (2.1)
- INFUVITE ADULT is supplied as a single dose and as a pharmacy bulk package.
Single Dose: Add one daily dose of 10 mL (5 mL from Vial 1 and 5 mL from Vial 2) to not less than 500 mL, and preferably 1000 mL, of intravenous dextrose, saline or similar infusion solutions. (2.2)
Pharmacy Bulk Package: Add the contents of Vial 1 to the contents of Vial 2. This provides ten 10 mL daily doses. Take 10 mL from Vial 2 and add to not less than 500 mL, and preferably 1000 mL, of intravenous dextrose, saline or similar infusion solutions. (2.2)
- After dilution in an intravenous infusion, refrigerate resulting solution unless used immediately. Use solution within 24 hours after dilution (2.2)
- Monitor blood vitamin concentrations (2.3)
- See Full Prescribing Information for drug incompatibilities (2.4)

3 DOSAGE FORMS AND STRENGTHS

- INFUVITE ADULT supplied as single dose is an injection consisting of two vials labeled Vial 1 (5 mL) and Vial 2 (5 mL) (3)
- INFUVITE ADULT supplied as a pharmacy bulk package is an injection consisting of two vials labeled Vial 1 (50 mL) and Vial 2 (50 mL fill in 100 mL Vial) (3)

4 CONTRAINDICATIONS

- Hypersensitivity to any of the vitamins or excipients (4)
- Existing hypervitaminosis (4)

5 WARNINGS AND PRECAUTIONS

- Risk of Aluminum Toxicity: For at risk patients (renal failure or those with prolonged therapy), consider periodic monitoring of aluminum levels (5.1)
- Allergic Reactions: To thiamine may occur (5.2)
- Hypervitaminosis A: Patients with renal failure or liver disease may be at higher risk (5.3)
- Decreased Anticoagulant Effect of Warfarin: Monitor INR (5.4, 7.1)
- Interferes with Megaloblastic Anemia Diagnosis: Avoid during testing for this disorder (5.5)
- Risk of Vitamin Deficiencies or Excesses: Monitor blood vitamin concentrations (5.6)
- False Negative Urine Glucose Tests: Due to vitamin C (5.7)

6 ADVERSE REACTIONS

Adverse reactions have included anaphylaxis and anaphylactoid reactions including shortness of breath, wheezing and angioedema, rash, erythema, pruritis, headache, dizziness, agitation, anxiety, diplopia (6)

To report SUSPECTED ADVERSE REACTIONS, contact Sandoz Inc. at 1-800-525-8747 or FDA at 1-800-FDA-1088 or www.fda.gov/medwatch

7 DRUG INTERACTIONS

Effect of INFUVITE ADULT on other drugs:

- Antibiotics: Thiamine, riboflavin, pyridoxine, niacinamide, and ascorbic acid decrease activities of erythromycin, kanamycin, streptomycin, doxycycline, and lincomycin (7.1)
- Bleomycin: Ascorbic acid and riboflavin may reduce the activity of bleomycin (7.1)
- Levodopa: Pyridoxine may decrease blood levels of levodopa and levodopa efficacy may decrease (7.1)
- Phenytoin: Folic acid may decrease phenytoin blood levels and increase risk of seizure activity (7.1)
- Methotrexate: Folic acid may decrease response to methotrexate (7.1)

Effects of other drugs on INFUVITE ADULT:

- Hydralazine, Isoniazid: Concomitant administration of hydralazine or isoniazid may increase pyridoxine requirements (7.2).
- Phenytoin: May decrease folic acid concentrations (7.2)
- Chloramphenicol: In patients with pernicious anemia, the hematologic response to vitamin B12 therapy may be inhibited (7.2)

8 USE IN SPECIFIC POPULATIONS

- Pregnant and Nursing Women: Requirements may exceed those of nonpregnant or nonlactating women (8.1, 8.3)
- Renal Impairment: Monitor renal function, calcium, phosphorus and vitamin A levels in patients with renal impairment (8.6)
- Hepatic Impairment: Monitor vitamin A level in patients with liver disease, high alcohol consumption (8.7)

FULL PRESCRIBING INFORMATION

1 INDICATIONS AND USAGE

INFUVITE ADULT is a combination of vitamins indicated for the prevention of vitamin deficiency in adults and children aged 11 and older receiving parenteral nutrition.

The physician should not await the development of clinical signs of vitamin deficiency before initiating vitamin therapy.

2 DOSAGE AND ADMINISTRATION

2.1 Important Dosage Instructions

INFUVITE ADULT is a combination product that contains the following vitamins: ascorbic acid, vitamin A, vitamin D, thiamine, riboflavin, pyridoxine, niacinamide, dexpanthenol, vitamin E, vitamin K1, folic acid, biotin, and vitamin B12.

INFUVITE ADULT is supplied as a single dose or as a pharmacy bulk package for intravenous use intended for administration by intravenous infusion after dilution.

INFUVITE ADULT Single Dose:

- Provides one daily dose of 10 mL (5 mL of Vial 1 plus 5 mL of Vial 2) which must be diluted prior to intravenous administration [see Dosage and Administration (2.2)].

INFUVITE ADULT Pharmacy Bulk Package:

- Provides ten 10 mL daily doses when the content of vial 1 is transferred into the content of vial 2. One 10 mL dose is then added directly to intravenous fluid. Pharmacy bulk package of INFUVITE ADULT is intended for dispensing of single doses to multiple patients in a pharmacy admixture program and is restricted to the preparation of admixtures for infusion [see Dosage and Administration (2.2)].

Patients with multiple vitamin deficiencies or with increased vitamin requirements may need multiple daily dosages as indicated. Some patients do not maintain adequate levels of certain vitamins when this formulation in recommended amounts is the only source of vitamins.

2.2 Preparation and Administration Instructions

Do not administer INFUVITE ADULT as a direct, undiluted intravenous injection as it may cause dizziness, faintness, and possible tissue irritation.

INFUVITE ADULT Single Dose:

- Use only in a suitable work area such as a laminar flow hood (or an equivalent clean air compounding area).
- Add 5 mL of Vial 1 and 5 mL of Vial 2 to at least 500 mL to 1000 mL, of intravenous dextrose or saline solutions.
- Discard unused portion.
- Visually inspect for particulate matter and discoloration prior to administration.
- After INFUVITE ADULT is diluted in an intravenous infusion, refrigerate the resulting solution unless it is to be used immediately, and use the solution within 24 hours after dilution.
- Minimize exposure to light because some of the vitamins in INFUVITE ADULT, particularly A, D and riboflavin, are light sensitive.

INFUVITE ADULT Pharmacy Bulk Package:

- Use only in a suitable work area such as a laminar flow hood (or an equivalent clean air compounding area).
- Transfer the contents of Vial 1 into the contents of Vial 2 to provide ten 10 mL single doses.
- Each bulk vial closure shall be penetrated only one time with a suitable sterile transfer device or dispensing set that allows measured dispensing of the contents.
- Once the closure system has been penetrated, complete dispensing from the pharmacy bulk vial should be completed within 4 hours. The mixed solution may be refrigerated and stored for up to 4 hours.
- Discard unused portion.
- Visually inspect for particulate matter and discoloration prior to administration.
- One daily 10 mL dose should be added directly to at least 500 mL to 1000 mL, of intravenous dextrose, saline or similar infusion solutions.
- After INFUVITE ADULT is diluted in an intravenous infusion, refrigerate the resulting solution unless it is to be used immediately, and use the solution within 24 hours after dilution.
- Minimize exposure to light because some of the vitamins in INFUVITE ADULT, particularly A, D and riboflavin, are light sensitive.

2.3 Monitoring Vitamin Blood Levels

Blood vitamin concentrations should be monitored to ensure maintenance of adequate levels, particularly in patients receiving parenteral multivitamins as the only source of vitamins for long periods of time.

2.4 Drug Incompatibilities

- INFUVITE ADULT is not physically compatible with moderately alkaline solutions such as a sodium bicarbonate solution and other alkaline drugs such as acetazolamide sodium, aminophylline, ampicillin sodium, tetracycline HCl and chlorothiazide sodium.
- Folic acid is unstable in the presence of calcium salts such as calcium gluconate.
- Vitamin A and thiamine in INFUVITE ADULT may react with bisulfite solutions such as sodium bisulfite or vitamin K bisulfate.
- Do not add INFUVITE ADULT directly to intravenous fat emulsions.
- Consult appropriate references for additional listings of physical and chemical compatibility of solutions and drugs with the vitamin infusion when needed. If incompatibilities are identified, avoid admixture or Y-site administration with vitamin solutions.

3 DOSAGE FORMS AND STRENGTHS

INFUVITE ADULT Single Dose: is an injection for intravenous administration consisting of two vials labeled Vial 1 (5 mL) and Vial 2 (5 mL). For the vitamin strengths [see Description (11)].

INFUVITE ADULT Pharmacy Bulk Package: is an injection for intravenous administration consisting of two vials labeled Vial 1 (50 mL) and Vial 2 (50 mL Fill in 100 mL Vial). The mixed solution (100 mL) will provide ten 10 mL single doses. For the vitamin strengths [see Description (11)].

4 CONTRAINDICATIONS

INFUVITE ADULT is contraindicated in patients who have

- An existing hypervitaminosis, or
- A history of hypersensitivity due to any vitamins or excipients contained in this formulation.

5 WARNINGS AND PRECAUTIONS

5.1 Aluminum Toxicity

INFUVITE ADULT contains aluminum that may be toxic. Aluminum may reach toxic levels with prolonged parenteral administration if kidney function is impaired. Premature neonates are particularly at risk because their kidneys are immature, and they require large amounts of calcium and phosphate solution, which contain aluminum.

Research indicates that patients with impaired kidney function, including premature neonates who receive parenteral levels of aluminum at greater than 4 to 5 mcg/kg/day accumulate aluminum at levels associated with central nervous system and bone toxicity. Tissue loading may occur at even lower rates of administration. To prevent aluminum toxicity periodically monitor aluminum levels with prolonged parenteral administration of INFUVITE ADULT in patients with renal impairment.

5.2 Allergic Reactions to Thiamine

Allergic reactions such as urticaria, shortness of breath, wheezing and angioedema have been reported following intravenous administration of thiamine, which is found in INFUVITE ADULT. There have been rare reports of anaphylactoid reactions following intravenous doses of thiamine. No fatal anaphylactoid reactions associated with INFUVITE ADULT have been reported.

5.3. Hypervitaminosis A

Hypervitaminosis A, manifested by nausea, vomiting, headache, dizziness, blurred vision has been reported in patients with renal failure receiving 1.5 mg/day retinol and in patients with liver disease, Therefore, supplementation of renal failure patients and patients with liver disease with vitamin A, an ingredient found in INFUVITE ADULT, should be undertaken with caution [See Use in Specific Populations (8.6, 8.7)].

5.4 Decreased Anticoagulant Effect of Warfarin

INFUVITE ADULT contains Vitamin K, which may decrease the anticoagulant action of warfarin. In patients who are on warfarin anticoagulant therapy receiving INFUVITE ADULT monitor blood levels of prothrombin/INR to determine if dose of warfarin needs to be adjusted.

5.5 Interference with Diagnosis of Megaloblastic Anemia

INFUVITE ADULT contains folic acid and cyanocobalamin which can mask serum deficiencies of folic acid and cyanocobalamin in patients with megaloblastic anemia. Avoid the use of INFUVITE ADULT in patients with suspected or diagnosed megaloblastic anemia prior to blood sampling for the detection of the folic acid and cyanocobalamin deficiencies.

5.6 Potential to Develop Vitamin Deficiencies or Excesses

In patients receiving parenteral multivitamins such as with INFUVITE ADULT, blood concentration should be periodically monitored to determine if deficiencies or excesses are developing. INFUVITE ADULT may not correct long-standing specific vitamin deficiencies. The administration of additional therapeutic doses of specific vitamins may be required [see Dosage and Administration (2.3)].

5.7 Interference with Urine Glucose Testing

INFUVITE ADULT contains vitamin C which is also known as ascorbic acid. Ascorbic acid in the urine may cause false negative urine glucose results.

6 ADVERSE REACTIONS

The following adverse reactions are discussed in greater detail in other section of the labeling.

- Allergic reactions to thiamine [see Warnings and Precautions (5.2)].
- Hypervitaminosis A [see Warnings and Precautions (5.3)]

The following adverse reactions have been identified during postapproval use of INFUVITE ADULT. Because these reactions are reported voluntarily from a population of uncertain size, it is not always possible to reliably estimate their frequency or establish a causal relationship to drug exposure.

Dermatologic: rash, erythema, pruritis

CNS: headache, dizziness, agitation, anxiety

Ophthalmic: diplopia

7 DRUG INTERACTIONS

A number of interactions between vitamins and drugs have been reported. The following are examples of these types of interactions:

7.1 Drug Interactions Affecting Co-administered Drugs

Warfarin: Vitamin K, a component of INFUVITE ADULT, antagonizes the anticoagulant action of warfarin. In patients who are co-administered warfarin and INFUVITE ADULT, blood levels of prothrombin/INR should be monitored to determine if dose of warfarin needs to be adjusted [see Warnings and Precautions (5.4)].

Antibiotics: Thiamine, riboflavin, pyridoxine, niacinamide, and ascorbic acid decrease antibiotic activities of erythromycin, kanamycin, streptomycin, doxycycline, and lincomycin.

Bleomycin: Ascorbic acid and riboflavin inactivate bleomycin in vitro, thus the activity of bleomycin may be reduced.

Levodopa: Pyridoxine may increase the metabolism of levodopa (decrease blood levels of levodopa) and decrease its efficacy.

Phenytoin: Folic acid may increase phenytoin metabolism and lower the serum concentration of phenytoin resulting in increased seizure activity.

Methotrexate: Folic acid may decrease a patient’s response to methotrexate therapy.

7.2 Drug Interactions Affecting Vitamin Levels

Hydralazine, Isoniazid: Concomitant administration of hydralazine or isoniazid may increase pyridoxine requirements.

Phenytoin: Phenytoin may decrease serum folic acid concentrations.

Chloramphenicol: In patients with pernicious anemia, the hematologic response to vitamin B12 therapy may be inhibited by chloramphenicol.

8 USE IN SPECIFIC POPULATIONS

8.1 Pregnancy

Pregnancy Category C

INFUVITE ADULT has not been studied in pregnant women. Pregnant women should follow the U.S. Recommended Daily Allowances for their condition, because their vitamin requirements may exceed those of nonpregnant women. Animal reproduction studies have not been conducted with INFUVITE ADULT.

8.3 Nursing Mothers

INFUVITE ADULT has not been studied in lactating women.Lactating women should follow the U.S. Recommended Daily Allowances for their condition, because their vitamin requirement may exceed those of nonlactating women. Caution should be exercised when INFUVITE ADULT is administered to a nursing mother.

8.4 Pediatric Use

Safety and effectiveness in children below the age of 11 years have not been established.

8.5 Geriatric Use

Safety and effectiveness for geriatric use have not been established.

8.6 Renal Impairment

INFUVITE ADULT has not been studied in patients with renal impairment. Monitor renal function, calcium, phosphorus and vitamin A levels in patients with renal impairment [see Warnings and Precautions (5.1, 5.3)].

8.7 Hepatic Impairment

INFUVITE ADULT has not been studied in patients with liver impairments. Monitor vitamin A level in patients with liver disease, high alcohol consumption [see Warnings and Precautions (5.3)].

10 OVERDOSAGE

Signs and symptoms of acute or chronic overdosage may be those of individual INFUVITE ADULT component toxicity. In postmarketed surveillance, overdosage with INFUVITE ADULT at two times the prescribed dose did not result in toxicity.

11 DESCRIPTION

INFUVITE ADULT (multiple vitamins injection) is a sterile product consisting of two vials provided as a single dose or as a pharmacy bulk package, both intended for intravenous use for administration by intravenous infusion after dilution:

INFUVITE ADULT Single Dose- two 5 mL single-dose vials labeled Vial 1 and Vial 2.

INFUVITE ADULT Pharmacy Bulk Package- two vials – 1 each of Vial 1 (50 mL) and Vial 2 (50 mL Fill in 100 mL Vial). The mixed solution (100 mL) will provide ten 10 mL single doses.

Each 5 mL of Vial 1 contains:

Ascorbic acid (Vitamin C) . . . . . . . . . . . . . . . . . . . . . . . . . . .200 mg

Vitamin A* (as palmitate) . . . . . . . . . . . . . . . . . . . . . . . . . .3,300 IU

Vitamin D3* (cholecalciferol) . . . . . . . . . . . . . . . . . . . . . . . . .200 IU

Thiamine (Vitamin B1) (as the hydrochloride) . . . . . . . . . . . . . 6 mg

Riboflavin (Vitamin B2)

(as riboflavin 5-phosphate sodium) . . . . . . . . . . . . . . . . . . . . .3.6 mg

Pyridoxine HCl (Vitamin B6) . . . . . . . . . . . . . . . . . . . . . . . . . . 6 mg

Niacinamide . . . . . . . . . . . . . . . . . . . . . . . . . . . . . . . . . . . . . . .40 mg

Dexpanthenol

(as d-pantothenyl alcohol) . . . . . . . . . . . . . . . . . . . . . . . . . . . .15 mg

Vitamin E* (dl-α-tocopheryl acetate) . . . . . . . . . . . . . . . . . . . 10 IU

Vitamin K1* . . . . . . . . . . . . . . . . . . . . . . . . . . . . . . . . . . . . .150 mcg

Inactive ingredients: 1.4% polysorbate 80, sodium hydroxide and/or hydrochloric acid for pH adjustment, and water for injection.

*Polysorbate 80 is used to water solubilize the oil-soluble vitamins A, D, E, and K.

Each 5 mL of Vial 2 contains:

Folic acid . . . . . . . . . . . . . . . . . . . . . . . . . . . . . . . . . . . . .600 mcg

Biotin . . . . . . . . . . . . . . . . . . . . . . . . . . . . . . . . . . . . . . . . .60 mcg

Vitamin B12 (cyanocobalamin) . . . . . . . . . . . . . . . . . . . . . . 5 mcg

Inactive ingredients: 30% propylene glycol, citric acid and/or sodium citrate for pH adjustment, and water for injection.

INFUVITE ADULT makes available a combination of important oil-soluble and water-soluble vitamins in an aqueous solution, formulated for incorporation into intravenous solutions. The liposoluble vitamins A, D, E, and K have been solubilized in an aqueous medium with polysorbate 80, permitting intravenous administration of these vitamins.

Contains no more than 70 mcg/L of aluminum (combined Vials 1 and 2).

13 NONCLINICAL TOXICOLOGY

13.1 Carcinogenesis, Mutagenesis, Impairment of Fertility

Carcinogenicity, mutagenicity, and fertility studies have not been performed with INFUVITE ADULT.

16 HOW SUPPLIED/STORAGE AND HANDLING

How Supplied:

INFUVITE ADULT (multiple vitamins injection) is supplied as follows:

INFUVITE ADULT Single Dose:

- NDC 54643-9007-1 - Boxes containing ten single-dose vials—five each of Vial 1 (5 mL) and Vial 2 (5 mL), one Vial 1 plus one Vial 2 to be used for a single dose [see Dosage and Administration (2.1)].

INFUVITE ADULT Pharmacy Bulk Package:

- NDC 54643-9015-2 - Boxes containing 2 vials – 1 each of Vial 1 (50 mL) and Vial 2 (50 mL Fill in 100 mL Vial). Mix contents of Vial 1 with Vial 2 to provide 10 single doses [see Dosage and Administration (2.1)].

Storage and Handling:

Minimize exposure of INFUVITE ADULT to light because vitamins A, D and riboflavin are light sensitive.

Store under refrigeration, 2° to 8°C (36° to 46°F).

17 PATIENT COUNSELING INFORMATION

Instruct patients (if age appropriate) and caregivers:

- To watch for signs of allergic reactions such as urticaria, shortness of breath, wheezing and angioedema since hypersensitivity reactions may occur to any of the vitamins or excipients contained in INFUVITE ADULT.
- To watch for and immediately report nausea, vomiting, headache, dizziness, blurred vision, especially if patients have renal impairment, as these may be signs of hypervitaminosis A.
- To report other adverse reactions such as rash, erythema, pruritus, headache, dizziness, agitation, anxiety, and diplopia.
- That the patients on warfarin anticoagulant therapy will be monitored periodically with blood prothrombin/ INR levels to determine if their dose of warfarin needs to be adjusted.
- About the significance of periodic monitoring of blood vitamin concentrations to determine if vitamin deficiencies or excesses are developing and the need to monitor renal function, calcium, phosphorus, aluminum and vitamin A levels in patients with renal impairment.
- That INFUVITE ADULT should be avoided in patients with suspected or diagnosed megaloblastic anemia prior to blood sampling for the detection of the folic acid and cyanocobalamin deficiencies.
- That vitamin C (ascorbic acid) contained in INFUVITE ADULT may cause false negative urine glucose results.

Manufactured by

Sandoz Canada Inc.

145 Jules-Léger Street

Boucherville, Qc, Canada, J4B 7K8

Distributed by

Baxter Healthcare Corporation for NOVAPLUS®

Clintec Nutrition Division

Deerfield, IL 60015 USA

Printed in Canada

NOVAPLUS® is a registered trademark of Vizient, Inc.

® INFUVITE is a registered trademark of Sandoz Canada Inc.

46194734

10-2016

Infuvite Adult Single Dose Vials Carton

NDC 54643-9007-1 2A9018NP

INFUVITE® ADULT

Multiple Vitamins Injection

For Intavenous infusion after dilution only

Rx only

STERILE

Vial 1 (5 mL)
Vial 2 (5 mL)

Contains 5 each of Vial 1 (5 mL) and vial 2 (5 mL)

Store under refrigeration 2° to 8° C (36° to 46° F).

NOVAPLUS®

Infuvite Adult Pharmacy Bulk Package Carton

NDC 54643-9015-2 2A9019NP

INFUVITE® ADULT

PHARMACY BULK PACKAGE

Multiple Vitamins Injection

Rx only

STERILE

PHARMACY BULK PACKAGE

NOT FOR DIRECT INFUSION

Vial 1

(50 mL)

Vial 2

(50 mL Fill in 100 mL Vial)

Both vials combined produce 10 single doses.

For intravenous infusion after dilution only.

Store under refrigeration 2° to 8° C (36° to 46° F).

NOVAPLUS®